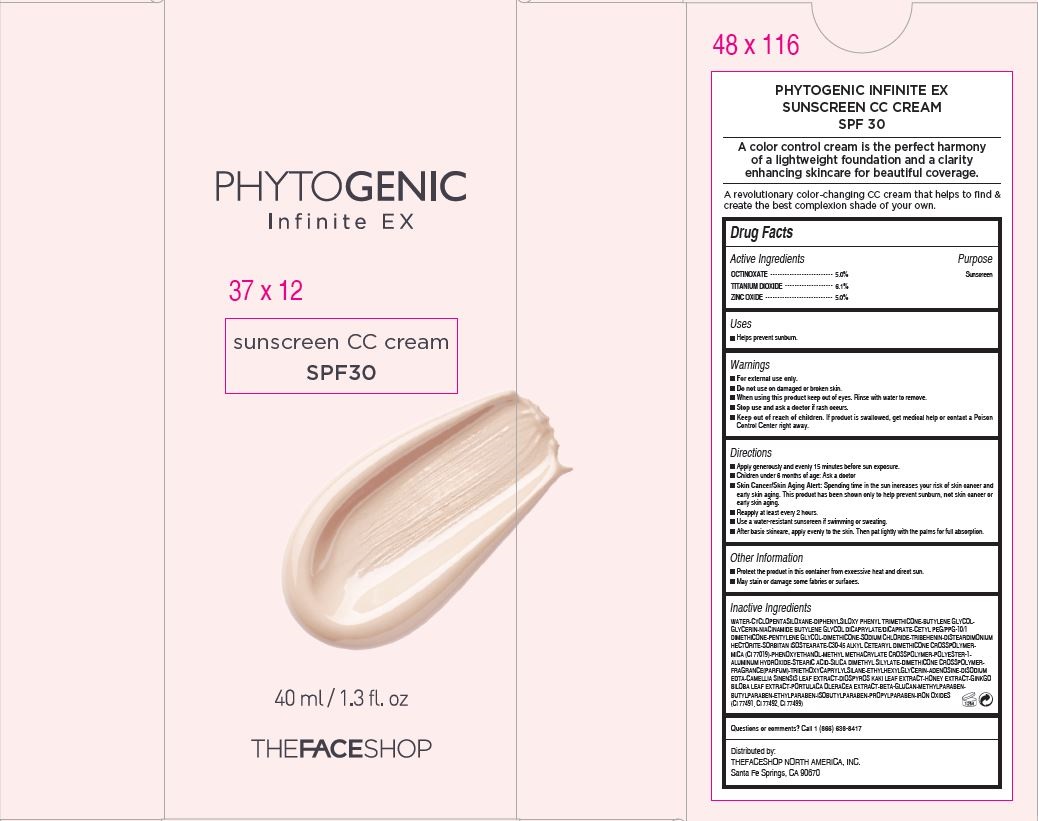 DRUG LABEL: PHYTOGENIC INFINTE
NDC: 51523-457 | Form: CREAM
Manufacturer: THEFACESHOP CO., LTD.
Category: otc | Type: HUMAN OTC DRUG LABEL
Date: 20141120

ACTIVE INGREDIENTS: ZINC OXIDE 2 g/40 mL; OCTINOXATE 2 g/40 mL; TITANIUM DIOXIDE 2.4 g/40 mL
INACTIVE INGREDIENTS: WATER

PHYTOGENIC INFINTE 37100457

Active Ingredients

Octinoxate ................5.0 %

Titanium Dioxide......6.1 %

Zinc Oxide.................5.0 %

Purpose

Sunscreen

Sunscreen

Sunscreen

Warnings

For external use only.

Do not use on damaged or broken skin

When using this product keep out of eyes. Rinse with water to remove.

Stop use and ask a doctor if rash occurs.

Keep out of reach of children.

If product is swallowed, get medical help or contact a Poison Control Center right away.

Directions

Apply generously and evenly 15 minutes before sun exposure.
Children under 6 months of age: Ask a doctor
Skin Cancer/Skin Aging Alert: Spending time in the sun increases your risk of skin cancer and
early skin aging. This product has been shown only to help prevent sunburn, not skin cancer or
early skin aging.
Reapply at least every 2 hours.
Use a water-resistant sunscreen if swimming or sweating.
After basic skincare, apply evenly to the skin. Then pat lightly with the palms for full absorption.

Other Information

Protect the product in this container from excessive heat and direct sun.

May stain or damage some fabrics or surfaces

Inactive Ingredients

WATER•CYCLOPENTASILOXANE•DIPHENYLSILOXY PHENYL TRIMETHICONE•BUTYLENE GLYCOL•
GLYCERIN•NIACINAMIDE BUTYLENE GLYCOL DICAPRYLATE/DICAPRATE•CETYL PEG/PPG-10/1
DIMETHICONE•PENTYLENE GLYCOL•DIMETHICONE•SODIUM CHLORIDE•TRIBEHENIN•DISTEARDIMONIUM
HECTORITE•SORBITAN ISOSTEARATE•C30-45 ALKYL CETEARYL DIMETHICONE CROSSPOLYMER•
MICA (CI 77019)•PHENOXYETHANOL•METHYL METHACRYLATE CROSSPOLYMER•POLYESTER-1•
ALUMINUM HYDROXIDE•STEARIC ACID•SILICA DIMETHYL SILYLATE•DIMETHICONE CROSSPOLYMER•
FRAGRANCE(PARFUM)•TRIETHOXYCAPRYLYLSILANE•ETHYLHEXYLGLYCERIN•ADENOSINE•DISODIUM
EDTA•CAMELLIA SINENSIS LEAF EXTRACT•DIOSPYROS KAKI LEAF EXTRACT•HONEY EXTRACT•GINKGO
BILOBA LEAF EXTRACT•PORTULACA OLERACEA EXTRACT•BETA-GLUCAN•METHYLPARABEN•
BUTYLPARABEN•ETHYLPARABEN•ISOBUTYLPARABEN•PROPYLPARABEN•IRON OXIDES
(CI 77491, CI 77492, CI 77499)

Questions or comments? Call 1 (866) 638-8417

Distributed by:

THEFACESHOP NORTH AMERICA, INC.
Santa Fe Springs, CA 90670

PACKAGE LABEL

PHYTO GENIC

Infinite EX

CC cream

SPF 30 PA++